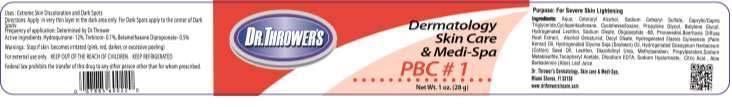 DRUG LABEL: DR. THROWERS PBC NO. 1
NDC: 69299-301 | Form: CREAM
Manufacturer: DR. THROWER'S SKINCARE, INC.
Category: prescription | Type: HUMAN PRESCRIPTION DRUG LABEL
Date: 20150522

ACTIVE INGREDIENTS: HYDROQUINONE 12 g/100 g; TRETINOIN 0.1 g/100 g; BETAMETHASONE DIPROPIONATE 0.5 g/100 g
INACTIVE INGREDIENTS: WATER; CETOSTEARYL ALCOHOL; SODIUM CETOSTEARYL SULFATE; MEDIUM-CHAIN TRIGLYCERIDES; CYCLOMETHICONE 5; CYCLOMETHICONE 6; PROPYLENE GLYCOL; BUTYLENE GLYCOL; HYDROGENATED SOYBEAN LECITHIN; SODIUM OLEATE; AMINO ACIDS; PROPANEDIOL; BOERHAVIA DIFFUSA ROOT; ALCOHOL; DECYL OLEATE; HYDROGENATED PALM KERNEL OIL; HYDROGENATED SOYBEAN OIL; HYDROGENATED COTTONSEED OIL; LECITHIN, SOYBEAN; DIAZOLIDINYL UREA; METHYLPARABEN; PROPYLPARABEN; SODIUM METABISULFITE; .ALPHA.-TOCOPHEROL ACETATE; EDETATE DISODIUM; HYALURONATE SODIUM; ANHYDROUS CITRIC ACID; ALOE VERA LEAF

DIRECTIONS:

APPLY IN A VERY THIN LAYER IN THE DARK AREA ONLY. FOR DARK SPOTS APPLY TO THE CENTER OF DARK SPOTS.

FREQUENCY OF APPLICATION: DETERMINED BY DR. THROWER.

USES:

EXTREME SKIN DISCOLORATION AND DARK SPOTS.

INGREDIENTS:

Aqua, Ceteraryl Alcohol, Sodium Cetearyl Sulfate, Caprylic/Capric Triglyceride,Cyclopentasiloxane, Cyclohexasiloxane, Propylene Glycol, Butylene Glycol , Hydrogenated Lecithin,Sodium Oleate , Oligopeptide-68, Propanediol, Boerhavia Diffusa Root Extract ,Alcohol Denatured, Decyl Oleate, Hydrogenated Elaesis Guineensis (Palm Kernal) Oil, Hydrogenated Glycine Soja (Soybean) Oil, Hydrogenated Gossypium Herbaceum (Cotton) Seed Oil, Lecithin, Diazolidinyl Urea , Methylparaben, Propylparaben,Sodium Metabisulfite, Tocopheryl Acetate, Disodium EDTA, Sodium Hyaluronate, , Citric Acid , Aloe Barbadensis (Aloe) Leaf Juice

WARNINGS

STOP USE IF SKIN BECOMES IRRITATED (PINK, RED DARKER, OR EXCESSIVE PEELING). FOR EXTERNAL USE ONLY. KEEP OUT OF REACH OF CHILDREN. FEDERAL LAW PROHIBITS THE TRANSFER OF THIS DRUG TO ANY OTHER PERSON OTHER THAN FOR WHOM IT IS PRESCRIBED.